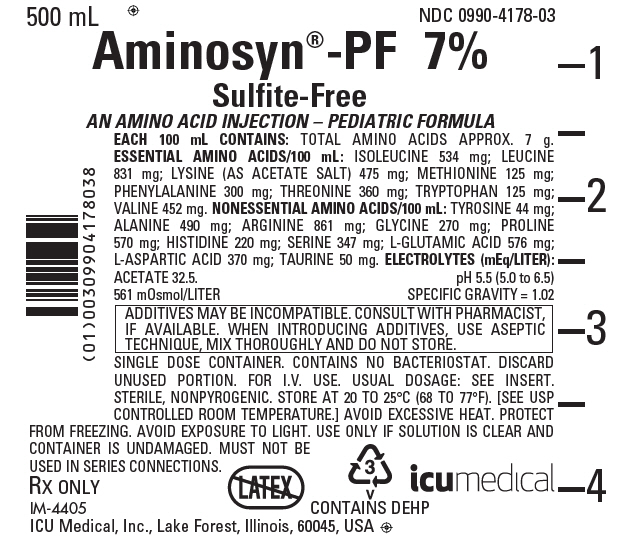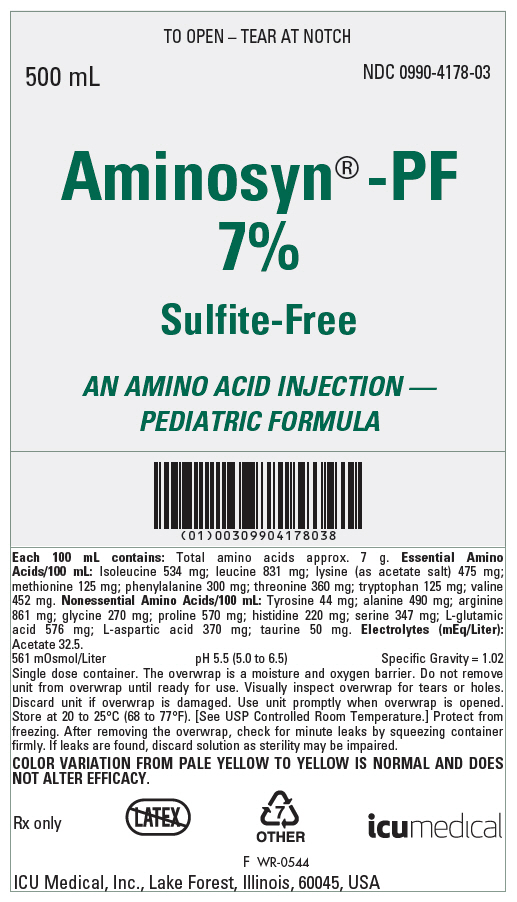 DRUG LABEL: Aminosyn-PF
NDC: 0990-4178 | Form: INJECTION, SOLUTION
Manufacturer: ICU Medical Inc.
Category: prescription | Type: HUMAN PRESCRIPTION DRUG LABEL
Date: 20251017

ACTIVE INGREDIENTS: ISOLEUCINE 534 mg/100 mL; LEUCINE 831 mg/100 mL; LYSINE ACETATE 475 mg/100 mL; METHIONINE 125 mg/100 mL; PHENYLALANINE 300 mg/100 mL; THREONINE 360 mg/100 mL; TRYPTOPHAN 125 mg/100 mL; VALINE 452 mg/100 mL; ALANINE 490 mg/100 mL; ARGININE 861 mg/100 mL; ASPARTIC ACID 370 mg/100 mL; GLUTAMIC ACID 576 mg/100 mL; GLYCINE 270 mg/100 mL; HISTIDINE 220 mg/100 mL; PROLINE 570 mg/100 mL; SERINE 347 mg/100 mL; TAURINE 50 mg/100 mL; TYROSINE 44 mg/100 mL
INACTIVE INGREDIENTS: WATER

Aminosyn® -PF 7%
Sulfite-Free

AN AMINO ACID INJECTION - PEDIATRIC FORMULA

Flexible Plastic Container

Rx only

DESCRIPTION

Aminosyn®-PF 7%, Sulfite-Free, (an amino acid injection — pediatric formula) is a sterile, nonpyrogenic solution for intravenous infusion. Aminosyn®-PF 7% is oxygen sensitive. The formulation is described below:

Aminosyn-PF 7%
An Amino Acid Injection — Pediatric Formula
Essential Amino Acids (mg/100 mL)
Isoleucine | 534
Leucine | 831
Lysine (acetate)* | 475
Methionine | 125
Phenylalanine | 300
Threonine | 360
Tryptophan | 125
Valine | 452

* Amount cited is for lysine alone and does not include the acetate salt.

Nonessential Amino Acids (mg/100 mL)
Alanine | 490
Arginine | 861
L-Aspartic Acid | 370
L-Glutamic Acid | 576
Glycine | 270
Histidine | 220
Proline | 570
Serine | 347
Taurine | 50
Tyrosine | 44

Electrolytes (mEq/L)
Sodium (Na^+) (mEq/L) | None
Potassium (K^+) (mEq/L) | None
Chloride (Clˉ) (mEq/L) | None
Acetate (C2H3O2ˉ)a (mEq/L) | 32.5

a From lysine acetate.

Product Characteristics
Protein Equivalent (Approx. grams/L) | 70
Total Nitrogen (grams/L) | 10.69
Osmolarity (mOsmol/L) | 561
pH (range) | 5.5 (5.0 to 6.5)

The formulas for the individual amino acids present in Aminosyn-PF 7% are as follows:

Essential Amino Acids
Isoleucine, USP | C6H13NO2
Leucine, USP | C6H13NO2
Lysine Acetate, USP | C6H14N2O2 • CH3COOH
Methionine, USP | C5H11NO2S
Phenylalanine, USP | C9H11NO2
Threonine, USP | C4H9NO3
Tryptophan, USP | C11H12N2O2
Valine, USP | C5H11NO2

Nonessential Amino Acids
Alanine, USP | C3H7NO2
Glycine, USP | C2H5NO2
Arginine, USP | C6H14N4O2
L-Aspartic Acid | C4H7NO4
 | HO2CCH2CH(NH2)CO2H
L-Glutamic Acid | C5H9NO4
 | HO2CCH2CHCH(NH2)CO2H
Histidine, USP | C6H9N3O2
Proline, USP | C5H9NO2
Serine, USP | C3H7NO3
Taurine | C2H7NO3S
Tyrosine, USP | C9H11NO3

The flexible plastic container is fabricated from a specially formulated polyvinylchloride. Water can permeate from inside the container into the overwrap but not in amounts sufficient to affect the solution significantly.

Solutions in contact with the plastic container may leach out certain chemical components from the plastic in very small amounts; however, biological testing was supportive of the safety of the plastic container materials.

Exposure to temperatures above 25°C/77°F during transport and storage will lead to minor losses in moisture content. Higher temperatures lead to greater losses. It is unlikely that these minor losses will lead to clinically significant changes within the expiration period.

CLINICAL PHARMACOLOGY

Aminosyn-PF 7% Sulfite-Free, (an amino acid injection — pediatric formula) contains a mixture of essential and nonessential amino acids as well as taurine. The amino acid composition has been specifically formulated to provide a well-tolerated nitrogen source for nutritional support and therapy for infants and young children. When administered in conjunction with a cysteine hydrochloride additive, Aminosyn-PF 7% results in plasma amino acid concentrations approximating a profile consistent with that of a breast-fed infant.

The rationale for Aminosyn-PF 7% is based on the observation of inadequate levels of essential amino acids in the plasma of infants receiving total parenteral nutrition (TPN) using conventional amino acid solutions.

Clinical studies in infants who required TPN therapy showed that infusion of Aminosyn-PF 7% resulted in plasma amino acid concentrations approximating those of normal breast or formula fed infants. In addition, weight gains, nitrogen balance, and serum protein concentrations were consistent with an improving nutritional status.

When infused with hypertonic dextrose as a calorie source, supplemented with cysteine hydrochloride, electrolytes, vitamins, and minerals, Aminosyn-PF 7% provides TPN for infants and young children, with the exception of essential fatty acids.

It is thought that the acetate from lysine acetate under the conditions of parenteral nutrition, does not impact net acid-base balance when renal and respiratory functions are normal. Clinical evidence seems to support this thinking; however, confirmatory experimental evidence is not available. The amounts of sodium and acetate in Aminosyn-PF 7% are not of clinical significance.

The addition of a cysteine hydrochloride additive will contribute to the chloride load.

The electrolyte content of any additives that are introduced should be carefully considered and included in input computations.

The human newborn conjugates bile with taurine which becomes the primary method of biliary excretion. Taurine deficiency because of its effect on bile salt conjugation and, therefore, on bile salt flow may be of major importance in the genesis of cholestasis. Taurine has also been shown to play a role in central nervous system development.

INDICATIONS AND USAGE

Aminosyn-PF 7%, Sulfite-Free, (an amino acid injection — pediatric formula) is indicated for the nutritional support of infants (including those of low birth weight) and young children requiring TPN via either central or peripheral infusion routes. Parenteral nutrition with Aminosyn-PF 7% is indicated to prevent nitrogen and weight loss or treat negative nitrogen balance in infants and young children where (1) the alimentary tract by the oral gastrostomy, or jejunostomy route, cannot or should not be used or adequate protein intake is not feasible by these routes, (2) gastrointestinal absorption of protein is impaired; or (3) protein requirements are substantially increased as with extensive burns. Dosage, route of administration, and concomitant infusion of non-protein calories are dependent on various factors, such as nutritional and metabolic status of the patient, anticipated duration of parenteral nutrition support, and vein tolerance. See DOSAGE AND ADMINISTRATION for additional information.

Central Venous Infusion

Central venous infusion should be considered when amino acid solutions are to be admixed with hypertonic dextrose to promote protein synthesis in hypercatabolic or severely depleted infants or those requiring long-term parenteral nutrition.

Peripheral Parenteral Nutrition

For moderately catabolic or depleted patients in whom the central venous route is not indicated, diluted amino acid solutions mixed with 5 to 10% dextrose solutions may be infused by peripheral vein, supplemented, if desired, with fat emulsion.

CONTRAINDICATIONS

Aminosyn-PF 7%, Sulfite-Free, (an amino acid injection — pediatric formula) is contraindicated in patients with untreated anuria, hepatic coma, inborn errors of amino acid metabolism (including those involving branched chain amino acid metabolism such as maple syrup urine disease and isovaleric acidemia), or hypersensitivity to one or more amino acids present in the solution.

WARNINGS

Safe, effective use of parenteral nutrition requires a knowledge of nutrition as well as clinical expertise in recognition and treatment of the complications which can occur. FREQUENT EVALUATION AND LABORATORY DETERMINATIONS ARE NECESSARY FOR PROPER MONITORING OF PARENTERAL NUTRITION. Studies should include blood sugar, serum proteins, kidney and liver function tests, electrolytes, hemogram, carbon dioxide content, serum osmolalities, blood cultures, and blood ammonia levels.

Administration of amino acids in the presence of impaired renal function or gastrointestinal bleeding may augment an already elevated blood urea nitrogen. Patients with azotemia from any cause should not be infused with amino acids without regard to total nitrogen intake.

Administration of intravenous solutions can cause fluid and/or solute overload resulting in dilution of serum electrolyte concentrations, overhydration, congested states, or pulmonary edema. The risk of dilutional states is inversely proportional to the electrolyte concentrations of the solutions.

Administration of amino acid solutions to a patient with hepatic insufficiency may result in plasma amino acid imbalances, hyperammonemia, prerenal azotemia, stupor and coma.

Hyperammonemia is of special significance in infants, as its occurrence in the syndrome caused by genetic metabolic defects is sometimes associated, although not necessarily in a causal relationship, with mental retardation. This reaction appears to be dose-related and is more likely to develop during prolonged therapy. It is essential that blood ammonia be measured frequently in infants.

Conservative doses of amino acids should be given, dictated by the nutritional status of the patient. Should symptoms of hyperammonemia develop, amino acid dosage levels should be reduced and titrated against serum ammonia levels.

WARNING: This product contains aluminum that may be toxic. Aluminum may reach toxic levels with prolonged parenteral administration if kidney function is impaired. Premature neonates are particularly at risk because their kidneys are immature, and they require large amounts of calcium and phosphate solutions, which contain aluminum.

Research indicates that patients with impaired kidney function, including premature neonates, who receive parenteral levels of aluminum at greater than 4 to 5 mcg/kg/day accumulate aluminum at levels associated with central nervous system and bone toxicity. Tissue loading may occur at even lower rates of administration.

PRECAUTIONS

Clinical evaluation and periodic laboratory determinations are necessary to monitor changes in fluid balance, electrolyte concentrations, and acid-base balance during prolonged parenteral therapy or whenever the condition of the patient warrants such evaluation. Significant deviations from normal concentrations may require the use of additional electrolyte supplements.

Strongly hypertonic nutrient solutions should be administered via an intravenous catheter placed in a central vein, preferably the superior vena cava.

Care should be taken to avoid circulatory overload, particularly in patients with cardiac insufficiency.

Special care must be taken when giving hypertonic dextrose to a diabetic or pre-diabetic patient. To prevent severe hyperglycemia in such patients, insulin may be required.

Administration of glucose at a rate exceeding the patient's utilization rate may lead to hyperglycemia, coma, and death.

The effect of infusion of amino acids, without dextrose, upon carbohydrate metabolism of children is not known at this time. It is essential to provide adequate exogenous dextrose calories concurrently with amino acids. Administration of amino acids without carbohydrates may result in the accumulation of ketone bodies in the blood. Correction of this ketonemia may be achieved by the administration of carbohydrate.

Essential fatty acid deficiency (EFAD) is becoming increasingly recognized in patients on long term TPN (more than 5 days). The use of fat emulsion to provide 4 — 10% of total caloric intake as linoleic acid may prevent EFAD.

Peripheral administration of Aminosyn-PF 7%, Sulfite-Free, (an amino acid injection — pediatric formula) requires appropriate dilution and provision of adequate calories. Care should be taken to assure proper placement of the needle within the lumen of the vein. The venipuncture site should be inspected frequently for signs of infiltration. If venous thrombosis or phlebitis occurs, discontinue infusions or change infusion site and initiate appropriate treatment.

Extraordinary electrolyte losses such as may occur during protracted nasogastric suction, vomiting, diarrhea, or gastrointestinal fistula drainage may necessitate additional electrolyte supplementation.

Metabolic acidosis can be prevented or readily controlled by adding a portion of the cations in the electrolyte mixture as acetate salts and in the case of hyperchloremic acidosis, by keeping the total chloride content of the infusate to a minimum.

Aminosyn-PF 7% contains no chloride.

Aminosyn-PF 7% contains no added phosphorus. Patients, especially those with hypophosphatemia, may require the addition of phosphate. To prevent hypocalcemia, calcium supplementation should always accompany phosphate administration. To assure adequate intake, serum levels should be monitored frequently.

Aminosyn-PF 7% contains no more than 25 mcg/L of aluminum.

To minimize the risk of possible incompatabilities arising from mixing this solution with other additives that may be prescribed, the final infusate should be inspected for cloudiness or precipitation immediately after mixing, prior to administration, and periodically during administration.

SPECIAL PRECAUTIONS FOR
CENTRAL INFUSIONS

ADMINISTRATION BY CENTRAL VENOUS CATHETER SHOULD BE USED ONLY
BY THOSE FAMILIAR WITH THIS TECHNIQUE AND ITS COMPLICATIONS.

Central vein infusion (with added concentrated carbohydrate solutions) of amino acid solutions requires a knowledge of nutrition as well as clinical expertise in recognition and treatment of complications. Attention must be given to solution preparation, administration and patient monitoring. IT IS ESSENTIAL THAT A CAREFULLY PREPARED PROTOCOL, BASED ON CURRENT MEDICAL PRACTICES, BE FOLLOWED, PREFERABLY BY AN EXPERIENCED TEAM.

SUMMARY HIGHLIGHTS OF COMPLICATIONS (See also Current Medical Literature).

1. Technical
  The placement of a central venous catheter should be regarded as a surgical procedure. One should be fully acquainted with various techniques of catheter insertion. For details of technique and placement sites, consult the medical literature. X-ray is the best means of verifying catheter placement. Complications known to occur from the placement of central venous catheters are pneumothorax, hemothorax, hydrothorax, artery puncture and transection, injury to the brachial plexus, malposition of the catheter, formation of arteriovenous fistula, phlebitis, thrombosis and air and catheter emboli.
2. Septic
  The constant risk of sepsis is present during administration of total parenteral nutrition. It is imperative that the preparation of the solution and the placement and care of catheters be accomplished under strict aseptic conditions.
  Solutions should ideally be prepared in the hospital pharmacy under a laminar flow hood using careful aseptic technique to avoid inadvertent touch contamination. Solutions should be used promptly after mixing. Storage should be under refrigeration and limited to a brief period of time, preferably less than 24 hours.
  Administration time for a single container and set should never exceed 24 hours.
3. Metabolic
  The following metabolic complications have been reported with TPN administration: Metabolic acidosis and alkalosis, hypophosphatemia, hypocalcemia, osteoporosis, hyperglycemia and glycosuria, rebound hypoglycemia, osmotic diuresis and dehydration, elevated liver enzymes, hypo- and hypervitaminosis, electrolyte imbalances and hyperammonemia in children. Frequent evaluations are necessary especially during the first few days of therapy to prevent or minimize these complications.
  Administration of glucose at a rate exceeding the patient's utilization rate may lead to hyperglycemia, coma and death. CLINICAL EVALUATION AND LABORATORY DETERMINATIONS, AT THE DISCRETION OF THE ATTENDING PHYSICIAN ARE NECESSARY FOR PROPER MONITORING DURING ADMINISTRATION. Do not withdraw venous blood for blood chemistries through the peripheral infusion site, as interference with estimations of nitrogen-containing substances may occur. Blood studies should include glucose, urea nitrogen, serum electrolytes, ammonia, cholesterol, acid-base balance, serum proteins, kidney and liver function tests, osmolarity and hemogram. White blood count and blood cultures are to be determined if indicated. Urinary osmolality and glucose should be determined as necessary.

Pregnancy Category C

Animal reproduction studies have not been conducted with Aminosyn-PF 7%. It is also not known whether Aminosyn-PF 7% can cause fetal harm when administered to a pregnant woman or can affect reproduction capacity. Aminosyn-PF 7% should be given to a pregnant woman only if clearly needed.

ADVERSE REACTIONS

Local reactions consisting of erythema, phlebitis and thrombosis at the infusion site have occurred with peripheral intravenous infusion of amino acids particularly if other substances, such as antibiotics, are also administered through the same site. In such cases the infusion site should be changed promptly to another vein. Use of large peripheral veins, inline filters, and slowing the rate of infusion may reduce the incidence of local venous irritation. Electrolyte additives should be spread throughout the day. Irritating additive medications may need to be injected at another venous site.

Generalized flushing, fever and nausea also have been reported during peripheral infusions of amino acid solutions.

If an adverse reaction does occur, discontinue the infusion, evaluate the patient, institute appropriate therapeutic countermeasures and save the remainder of the fluid for examination if deemed necessary.

OVERDOSAGE

In the event of overhydration or solute overload, re-evaluate the patient and institute appropriate corrective measures. See WARNINGS and PRECAUTIONS.

DOSAGE AND ADMINISTRATION

The total daily dose of the solution depends on the daily protein requirements and on the patient's metabolic and clinical response.

Pediatric requirements for parenteral nutrition are constrained by the greater relative fluid requirements of the infant and greater caloric requirements per kilogram than in the adult.

The recommended intravenous dose of Aminosyn-PF 7%, Sulfite-Free, (an amino acid injection — pediatric formula) is up to 2.5 g amino acid/kg/day for infants up to 10 kg. For infants and children larger than 10 kg, the total daily dose of amino acids should be up to 25 g amino acids/day for the first 10 kg of body weight plus 1 to 1.25 g amino acid for each kg of body weight over 10 kg. Initial amino acid dosage levels of 1 g/kg/day may be increased gradually in increments of 0.5 g/kg/day to approximate desired intake levels.

Aminosyn-PF 7% should be diluted with dextrose prior to use. Nonprotein calories should constitute approximately 100 to 130 kcal/kg/day. Part of the nonprotein caloric requirement may be provided as lipid emulsion administered concurrently to provide up to 60% of daily calories at a dose not to exceed 4 g fat/kg/day. Fluid intake for the infant receiving central venous TPN should be approximately 125 mL/kg/day (range: 100 to 175 mL/kg/day), depending on the clinical condition of the patient. Premature infants with respiratory distress syndrome suspected of having a patent ductus arteriosus should be given fluids more cautiously.

Cysteine is considered to be an essential amino acid for infants, especially preterm infants with potentially immature enzyme pathways. Therefore, addition of a cysteine supplement to the TPN admixture is recommended. The intake of cysteine by the preterm infant ingesting maternal milk is approximately 78 mg/kg/day. The suggested intravenous dosage level for Cysteine Hydrochloride Injection, USP is 500 mg (10 mL) for every 12.5 g (179 mL) of Aminosyn-PF 7% administered (see package insert for Cysteine Hydrochloride Injection, USP). In order to avoid potential insolubility of cysteine hydrochloride in admixtures, the foregoing concentration should not be exceeded.

In many patients, provision of adequate calories in the form of hypertonic dextrose may require the administration of exogenous insulin to prevent hyperglycemia and glycosuria. To prevent rebound hypoglycemia, a solution containing 5% dextrose should be administered when hypertonic dextrose solutions are abruptly discontinued.

SERUM ELECTROLYTES SHOULD BE MONITORED FREQUENTLY. Electrolytes may be added to the nutrient solution as indicated by the patient's clinical condition and laboratory determinations of plasma values. Major electrolytes are sodium, chloride, potassium, phosphate, magnesium and calcium. Daily administration of intravenous vitamin supplements including a complete complement of fat and water-soluble vitamins is required. Trace metal additives including zinc, copper, manganese, and chromium should also be provided, especially when long-term parenteral therapy is anticipated.

Calcium and phosphorus are added to the solution as indicated.

Potentially incompatible ions such as calcium and phosphate may be added to alternate infusate bottles to avoid precipitation. In patients with hyperchloremic or other metabolic acidosis, sodium and potassium may be added as the acetate or lactate salts to provide bicarbonate alternates. Bicarbonate should not be administered during infusion of the nutritional solution unless deemed absolutely necessary.

Additives may be incompatible. Consult with pharmacist, if available. When introducing additives, use aseptic technique, mix thoroughly and do not store.

To ensure the precise delivery of the small volumes of fluid necessary for total parenteral nutrition in infants, accurately calibrated and reliable infusion systems should be used.

Central Venous Nutrition

Hypertonic mixtures of amino acids and dextrose may be safely administered by continuous infusion through a central venous catheter with the tip located in the superior vena cava. Initial infusion rates should be slow, and gradually increased to the recommended 60-125 mL per kilogram body weight per day. If administration rate should fall behind schedule, no attempt to "catch up" to planned intake should be made. In addition to meeting protein needs, the rate of administration, particularly during the first few days of therapy, is governed by the patient's glucose tolerance. Daily intake of amino acids and dextrose should be increased gradually to the maximum required dose as indicated by frequent determinations of glucose levels in blood and urine.

Peripheral Parenteral Nutrition

For patients in whom the central venous route is not indicated and who can consume adequate calories enterally, Aminosyn-PF 7% may be administered by peripheral vein with parenteral nonprotein calories. The concentration of dextrose in the final admixture is 5 to 10%, and simultaneous administration of lipid emulsion is recommended both as a calorie source and to attenuate the potentially irritating effects of the hypertonic nutritional admixture. Fat emulsion may comprise up to 60% of the daily caloric intake at a dosage level not to exceed 4 g fat/kg/day. It is essential that peripheral infusion be accompanied by adequate caloric intake.

Parenteral drug products should be inspected visually for particulate matter and discoloration prior to administration, whenever solution and container permit. COLOR VARIATION FROM PALE YELLOW TO YELLOW IS NORMAL AND DOES NOT ALTER EFFICACY.

WARNING: Do not use flexible container in series connections.

HOW SUPPLIED

NDC No. | Concentration | Container (mL)
0409-4178-03 | Aminosyn-PF 7%, Sulfite-Free, (an amino acid injection - | 500
0990-4178-03 | pediatric formula) | 500

ICU Medical is transitioning NDC codes from the "0409" to a "0990" labeler code. Both NDC codes are expected to be in the market for a period of time.

Store at 20 to 25ºC (68 to 77ºF). [See USP Controlled Room Temperature.] Protect from freezing. Avoid exposure to light.

Revised: August, 2018

EN-4682

ICU Medical, Inc., Lake Forest, Illinois, 60045 USA

PRINCIPAL DISPLAY PANEL - 500 mL Bag Label

500 mL
NDC 0990-4178-03

Aminosyn®-PF 7%
Sulfite-Free
AN AMINO ACID INJECTION – PEDIATRIC FORMULA

EACH 100 mL CONTAINS: TOTAL AMINO ACIDS APPROX. 7 g.
ESSENTIAL AMINO ACIDS/100 mL : ISOLEUCINE 534 mg; LEUCINE
831 mg; LYSINE (AS ACETATE SALT) 475 mg; METHIONINE 125 mg;
PHENYLALANINE 300 mg; THREONINE 360 mg; TRYPTOPHAN 125 mg;
VALINE 452 mg. NONESSENTIAL AMINO ACIDS/100 mL: TYROSINE 44 mg;
ALANINE 490 mg; ARGININE 861 mg; GLYCINE 270 mg; PROLINE
570 mg; HISTIDINE 220 mg; SERINE 347 mg; L-GLUTAMIC ACID 576 mg;
L-ASPARTIC ACID 370 mg; TAURINE 50 mg. ELECTROLYTES (mEq/LITER):

ACETATE 32.5.
pH 5.5 (5.0 to 6.5)

561 mOsmol/LITER
SPECIFIC GRAVITY = 1.02

ADDITIVES MAY BE INCOMPATIBLE. CONSULT WITH PHARMACIST,
IF AVAILABLE. WHEN INTRODUCING ADDITIVES, USE ASEPTIC
TECHNIQUE, MIX THOROUGHLY AND DO NOT STORE.

SINGLE DOSE CONTAINER. CONTAINS NO BACTERIOSTAT. DISCARD
UNUSED PORTION. FOR I.V. USE. USUAL DOSAGE: SEE INSERT.
STERILE, NONPYROGENIC. STORE AT 20 TO 25°C (68 TO 77°F). [SEE USP
CONTROLLED ROOM TEMPERATURE.] AVOID EXCESSIVE HEAT. PROTECT
FROM FREEZING. AVOID EXPOSURE TO LIGHT. USE ONLY IF SOLUTION IS CLEAR AND
CONTAINER IS UNDAMAGED. MUST NOT BE
USED IN SERIES CONNECTIONS.

RX ONLY
IM-4405

3
v
CONTAINS DEHP
icumedical

ICU Medical, Inc., Lake Forest, Illinois, 60045, USA

PRINCIPAL DISPLAY PANEL - 500 mL Overwrap Label

TO OPEN – TEAR AT NOTCH

500 mL
NDC 0990-4178-03

Aminosyn®-PF
7%

Sulfite-Free

AN AMINO ACID INJECTION —
PEDIATRIC FORMULA

Each 100 mL contains: Total amino acids approx. 7 g. Essential Amino
Acids/100 mL: Isoleucine 534 mg; leucine 831 mg; lysine (as acetate salt) 475 mg;
methionine 125 mg; phenylalanine 300 mg; threonine 360 mg; tryptophan 125 mg; valine
452 mg. Nonessential Amino Acids/100 mL: Tyrosine 44 mg; alanine 490 mg; arginine
861 mg; glycine 270 mg; proline 570 mg; histidine 220 mg; serine 347 mg; L-glutamic
acid 576 mg; L-aspartic acid 370 mg; taurine 50 mg. Electrolytes (mEq/Liter):

Acetate 32.5.
561 mOsmol/Liter
pH 5.5 (5.0 to 6.5)
Specific Gravity = 1.02

Single dose container. The overwrap is a moisture and oxygen barrier. Do not remove
unit from overwrap until ready for use. Visually inspect overwrap for tears or holes.
Discard unit if overwrap is damaged. Use unit promptly when overwrap is opened.
Store at 20 to 25°C (68 to 77°F). [See USP Controlled Room Temperature.] Protect from
freezing. After removing the overwrap, check for minute leaks by squeezing container
firmly. If leaks are found, discard solution as sterility may be impaired.

COLOR VARIATION FROM PALE YELLOW TO YELLOW IS NORMAL AND DOES
NOT ALTER EFFICACY.

Rx only

7
OTHER

icumedical

F WR-0544

ICU Medical, Inc., Lake Forest, Illinois, 60045, USA